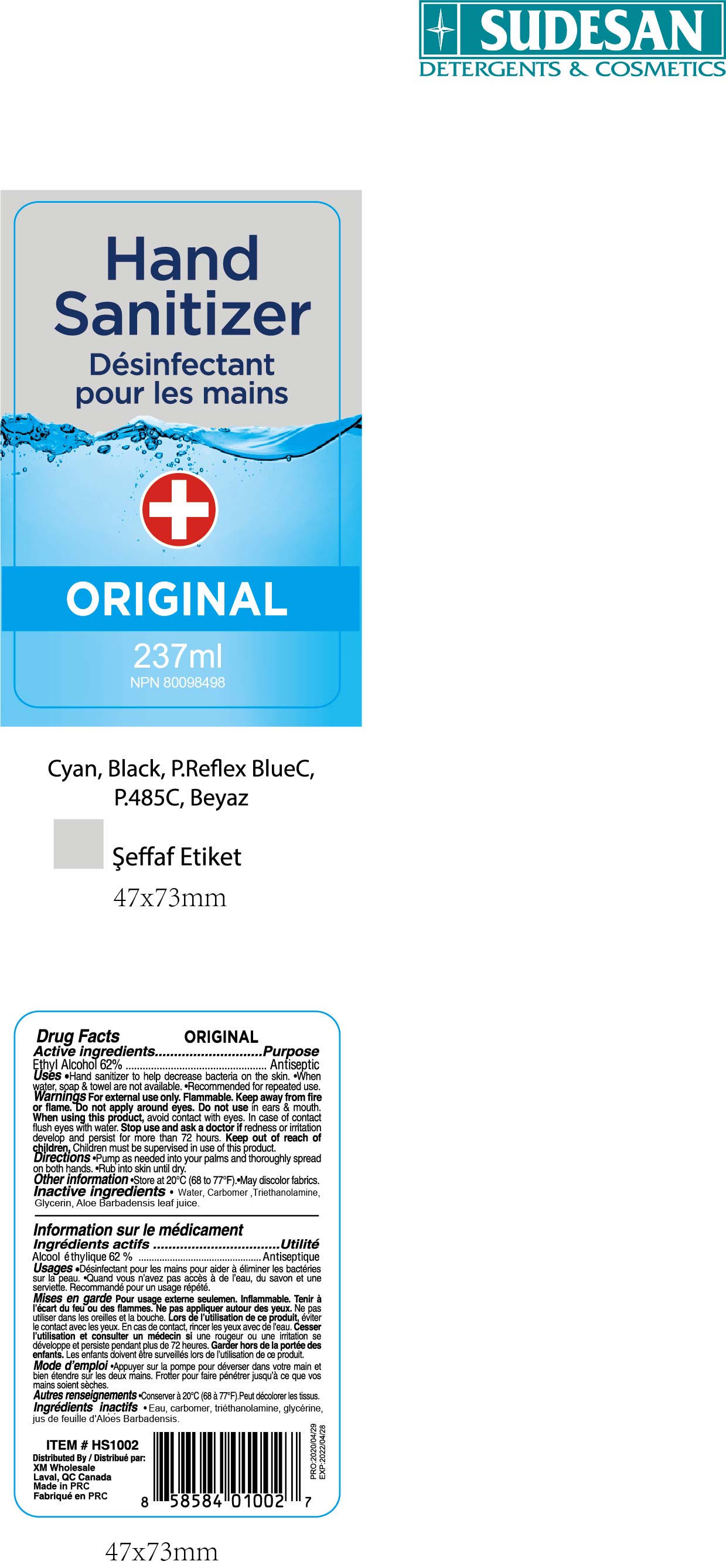 DRUG LABEL: SUDESAN Hand Sanitizer Original
NDC: 75112-002 | Form: SOLUTION
Manufacturer: Zhejiang Shenying Technology Co., Ltd. Jiaojiang Branch
Category: otc | Type: HUMAN OTC DRUG LABEL
Date: 20200522

ACTIVE INGREDIENTS: ALCOHOL 62 mL/100 mL
INACTIVE INGREDIENTS: GLYCEROL FORMAL; CARBOMER 934; TROLAMINE; TOCOPHEROL; ALOE VERA LEAF

NA

Active Ingredient(s)

Ethyl Alcohol 62%

Purpose

Antiseptic

Use

Hand sanitizer to help decrease bacterial on the skin

When water, soap and towel are not available

Recommended for repeated use

Warnings

For external use only. Flammable. Keep away from fire or flame.

Do not apply around eyes.

Do not use in ears and mouth.

When using this product, avoid contact with eyes. In case of contact, flush eyes with water

Stop use and ask a doctor if redness or irritation develop and persist for more than 72 hours

Keep out of reach of children. Children must be supervised in use of this products.

Directions

Pump as needed into your palms and thoroughly spread on both hands

Rub into skin until dry.

Other information

Store at 20C (68 to 77F)

May discolor fabrics

Inactive ingredients

Water, carbomer, triethanolamine, glycerol, aloe barbadensis leaf juice